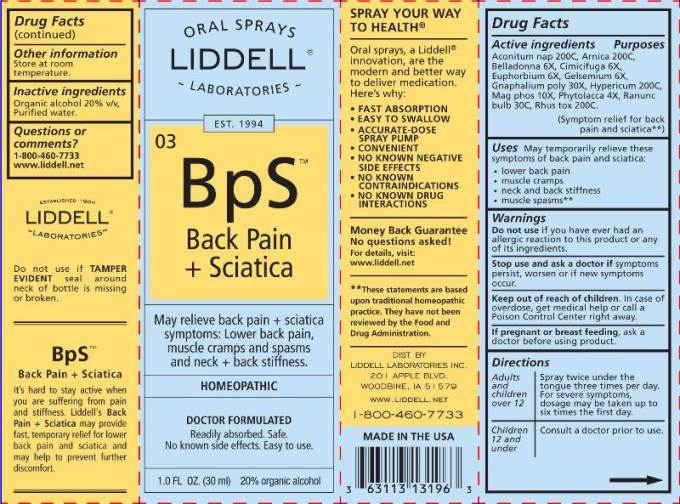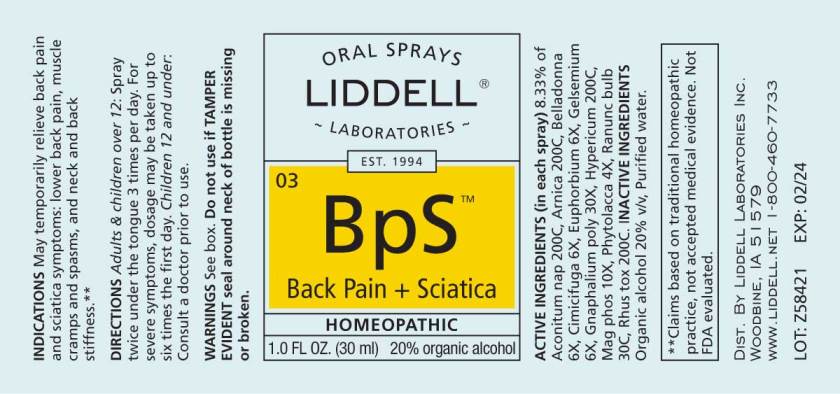 DRUG LABEL: Back Pain and Sciatica
NDC: 50845-0237 | Form: SPRAY
Manufacturer: Liddell Laboratories, Inc.
Category: homeopathic | Type: HUMAN OTC DRUG LABEL
Date: 20240701

ACTIVE INGREDIENTS: ACONITUM NAPELLUS WHOLE 200 [hp_C]/1 mL; ARNICA MONTANA WHOLE 200 [hp_C]/1 mL; ATROPA BELLADONNA 6 [hp_X]/1 mL; BLACK COHOSH 6 [hp_X]/1 mL; EUPHORBIA RESINIFERA RESIN 6 [hp_X]/1 mL; GELSEMIUM SEMPERVIRENS ROOT 6 [hp_X]/1 mL; PSEUDOGNAPHALIUM OBTUSIFOLIUM WHOLE 30 [hp_X]/1 mL; HYPERICUM PERFORATUM WHOLE 200 [hp_C]/1 mL; MAGNESIUM PHOSPHATE, DIBASIC TRIHYDRATE 10 [hp_X]/1 mL; PHYTOLACCA AMERICANA ROOT 4 [hp_X]/1 mL; RANUNCULUS BULBOSUS WHOLE 30 [hp_C]/1 mL; TOXICODENDRON PUBESCENS LEAF 200 [hp_C]/1 mL
INACTIVE INGREDIENTS: WATER; ALCOHOL

DRUG FACTS:

ACTIVE INGREDIENTS:

(in each spray) 8.33% of Aconitum napellus 200C, Arnica montana 200C, Belladonna 6X, Cimicifuga racemosa 6X, Euphorbium officinarum 6X, Gelsemium sempervirens 6X, Gnaphalium polycephalum 30X, Hypericum perforatum 200C, Magnesia phosphorica 10X, Phytolacca decandra 4X, Ranunculus bulbosus 30C, Rhus tox 200C.

(Symptom relief for back pain and sciatica**)

USES:

May temporarily relieve these symptoms of back pain and sciatica:

- lower back pain
- muscle cramps
- neck and back stiffness
- muscle spasms**

**Claims based on traditional homeopathic practice, not accepted medical evidence. Not FDA evaluated.

WARNINGS:

Do not use if you have ever had an allergic reaction to this product or any of its ingredients.

Stop use and ask a doctor if symptoms persist, worsen or if new symptoms occur.

Keep out of reach of children. In case of overdose, get medical help or call a Poison Control Center right away.

If pregnant or breast feeding, ask a doctor before using product.

Do not use if TAMPER EVIDENT seal around neck of bottle is missing or broken.

OTHER INFORMATION: Store at room temperature.

KEEP OUT OF REACH OF CHILDREN:

In case of overdose, get medical help or contact a Poison Control Center right away.

DIRECTIONS:

Adults and children over 12: Spray twice under the tongue three times per day. For severe symptoms, dosage may be taken up to six times the first day.

Children 12 and under: Consult a doctor prior to use.

INDICATIONS:

May temporarily relieve these symptoms of back pain and sciatica:

- lower back pain
- muscle cramps
- neck and back stiffness
- muscle spasms**

**Claims based on traditional homeopathic practice, not accepted medical evidence. Not FDA evaluated.

INACTIVE INGREDIENTS:

Organic alcohol 20% v/v, Purified water.

QUESTIONS:

DIST. BY:

LIDDELL LABORATORIES

201 APPLE BLVD.

WOODBINE, IA 51579

WWW.LIDDELL.NET

1-800-460-7733

PACKAGE LABEL DISPLAY:

ORAL SPRAYS
LIDDELL
LABORATORIES
EST. 1994

03 BpS
Back Pain
+ Sciatica

May relieve back pain + sciatica
symptoms: Lower back pain,
muscle cramps and spasms
and neck + back stiffness

HOMEOPATHIC
DOCTOR FORMULATED

Readily absorbed. Safe.
No known side effects. Easy to use.

1.0 FL OZ (30 ml)